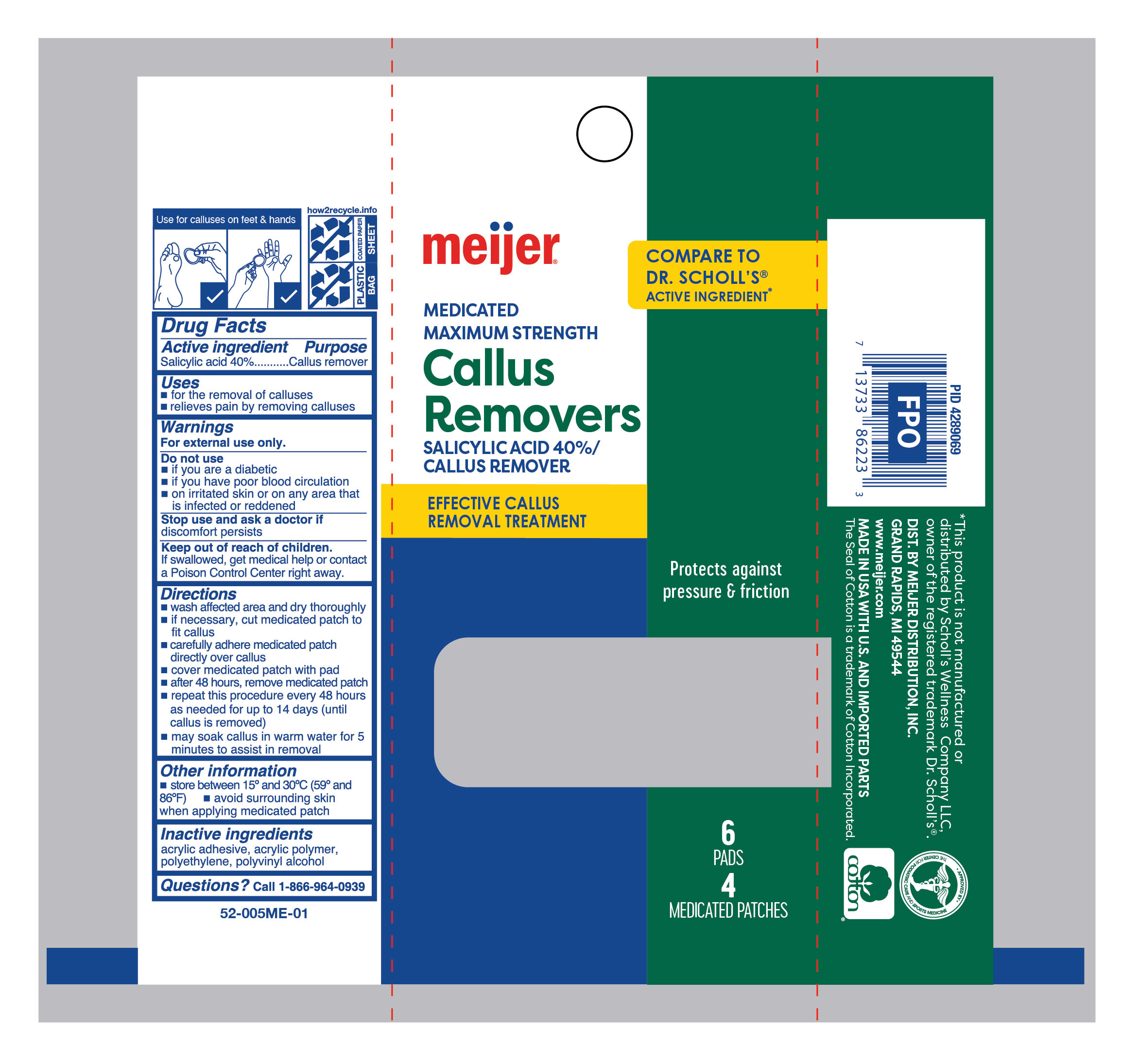 DRUG LABEL: Medicated Callus Removers
NDC: 79481-0609 | Form: PATCH
Manufacturer: Meijer Distribution Inc.
Category: otc | Type: HUMAN OTC DRUG LABEL
Date: 20251230

ACTIVE INGREDIENTS: SALICYLIC ACID 400 mg/1 g
INACTIVE INGREDIENTS: POLYVINYL ALCOHOL; HIGH DENSITY POLYETHYLENE

Meijer Medicated Callus Removers

Active ingredient

Salicylic acid 40%

Purpose

Callus remover

Uses

- for the removal of calluses
- relieves pain by removing calluses

Warnings

For external use only.

Do not use

- if you are diabetic
- if you have poor blood circulation
- on irritated skin,on any area that is infected or reddened

Ask your doctor

if discomfort persists.

Keep out of reach of children.

If swallowed, get medical help or contact a Poison Control Center right away.

Directions

- wash affected area and dry thoroughly
- if necessary, cut medicated patch to fit callus
- carefully adhere medicated patch directly over callus
- cover medicated patch with pad
- after 48 hours, remove medicated patch
- repeat procedure every 48 hours as needed for up to 14 days (until callus is removed)
- may soak callus in warm water for 5 minutes to assist in removal

Other information

- store between 15°C to 30°C (59° to 86°F)
- avoid surrounding skin when applying medicated patch

Inactive ingredients

acrylic adhesive, acrylic polymer, polyethylene, polyvinyl alcohol

Questions?

call 1-866-964-0939

Principal Display Panel

Meijer

Medicated

Maximum Strength

callus remover

SALICYLIC ACID 40%/

Callus Remover

Effective Callus Remover Treatment

Protects Against Pressure & Friction

6 PADS

4 MEDICATED PATCHES